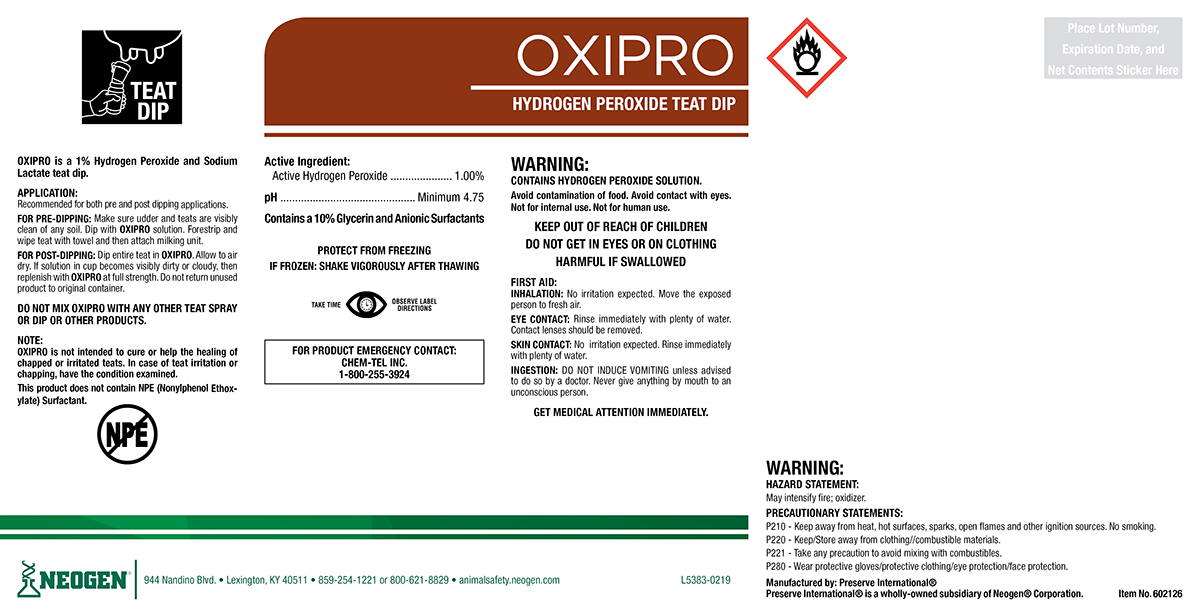 DRUG LABEL: OXIPRO
NDC: 60648-9010 | Form: SOLUTION
Manufacturer: Preserve International
Category: animal | Type: OTC ANIMAL DRUG LABEL
Date: 20190517

ACTIVE INGREDIENTS: HYDROGEN PEROXIDE 11.03 g/1 L; GLYCERIN 102.75 g/1 L

OXIPRO

DOSAGE AND ADMINISTRATION

OXIPRO is a 1% hydrogen Peroxide and Sodium Lactate teat dip.

APPLICATION:

Recommended for both pre and post dipping applications.

FOR PRE-DIPPING: Make sure udder and teats are visibly clean of any soil. Dip with OXIPRO solution. Forestrip and wipe teat with towel and then attach milking unit.

FOR POST-DIPPING: Dip Entire teat in OXIPRO.Allow to air dry. If solution in cup becomes visibly dirty or cloudy, then replenish with OXIPRO at full strength. Do not return unused product to original container.

DO NOT MIX OXIPRO WITH ANY OTHER TEAT SPRAY OR DIP OR OTHER PRODUCTS.

NOTE:

OXIPRO is not intended to cure or help the healing of chapped or irritated teats. In case of teat irritation or chapping, have the condition examined.

This product does not contain NPE (Nonylphenol Ethoxylate) Surfactant.

WARNINGS AND PRECAUTIONS

PROTECT FROM FREEZING

IF FROZEN: SHAKE VIGOROUSLY AFTER THAWING

WARNINGS AND PRECAUTIONS

TAKE TIME OBSERVE LABEL DIRECTIONS

WARNING:

CONTAINS HYDROGEN PEROXIDE SOLUTION

Avoid contamination of food. Avoid contact with eyes. Not for internal use. Not for human use.

KEEP OUT OF REACH OF CHILDREN

DO NOT GET IN EYES OR ON CLOTHING

HARMFUL IF SWALLOWED

FIRST AID:

INHALATION: No irritation expected. Move the exposed person to fresh air.

EYE CONTACT: Rinse immediately with plenty of water. Contact lenses should be removed.

SKIN CONTACT: No irritation expected. Rinse immediately with plenty of water.

INGESTION: DO NOT INDUCE VOMITING unless advised to do so by a doctor. Never give anything by mouth to an unconscious person.
GET MEDICAL ATTENTION IMMEDIATELY.

FOR PRODUCT EMERGENCY CONTACT: Chem-Tel Inc. 1-800-255-3924

HAZARD STATEMENTS:

May intensify fire; oxidizer.

PRECAUSTIONARY STATEMENTS:

P210 - Keep away from heat, hot surfaces, sparks, open flames and other ignition sources. No smoking.

P220 - Keep/Store away from clothing/combustible materials.

P221 - Take any precaution to avoid mixing with combustibles.

P280 - Wear protective gloves/protective clothing/eye protection/face protection.

PACKAGE LABEL

OXIPRO

HYDROGEN PEROXIDE TEAT DIP

Active Ingredients:

Active Hydrogen Peroxide..........1.00%
pH.....................................Minimum 4.75
Contains a 10% Glycerin and Anionic Surfactants

Manufactured By: Preserve International®

Preserve International® is a wholly-owned subsidiary of Neogen® Corporation.

NEOGEN®

944 Nandino Blvd.

Lexington, KY 40511

859-254-1221 or 800-621-8829

animalsafety.neogen.com